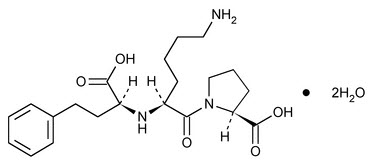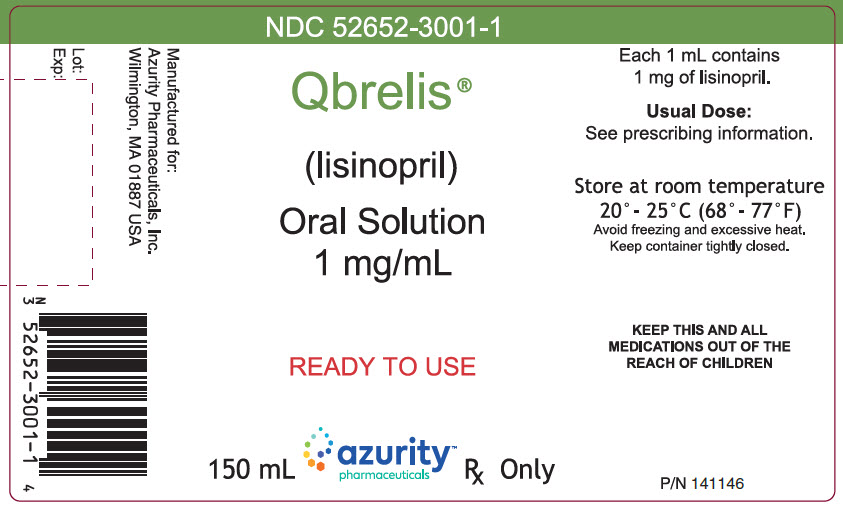 DRUG LABEL: Qbrelis
NDC: 52652-3001 | Form: SOLUTION
Manufacturer: Azurity Pharmaceuticals, Inc.
Category: prescription | Type: HUMAN PRESCRIPTION DRUG LABEL
Date: 20251216

ACTIVE INGREDIENTS: LISINOPRIL 1 mg/1 mL
INACTIVE INGREDIENTS: WATER; XYLITOL; SODIUM CITRATE, UNSPECIFIED FORM; CITRIC ACID MONOHYDRATE; SODIUM BENZOATE; HYDROCHLORIC ACID; SODIUM HYDROXIDE

HIGHLIGHTS OF PRESCRIBING INFORMATION

These highlights do not include all the information needed to use QBRELIS®safely and effectively. See full prescribing information for QBRELIS.
QBRELIS (lisinopril) oral solution
Initial U.S. Approval: 1988

WARNING: FETAL TOXICITY

See full prescribing information for complete boxed warning.

- When pregnancy is detected, discontinue QBRELIS as soon as possible (5.1).
- Drugs that act directly on the renin-angiotensin system can cause injury and death to the developing fetus (5.1).

1 INDICATIONS AND USAGE

QBRELIS is an angiotensin converting enzyme (ACE) inhibitor indicated for:

- Treatment of hypertension in adults and pediatric patients 6 years of age and older (1.1).
- Adjunct therapy for heart failure (1.2).
- Treatment of Acute Myocardial Infarction (1.3).

2 DOSAGE AND ADMINISTRATION

- Hypertension: Initial adult dose is 10 mg once daily. Titrate up to 40 mg daily based on blood pressure response. Initiate patients on diuretics at 5 mg once daily (2.1).
- Pediatric patients with glomerular filtration rate > 30 mL/min/1.73m^2: Initial dose in patients 6 years of age and older is 0.07 mg per kg (up to 5 mg total) once daily (2.1).
- Heart Failure: Initiate with 5 mg once daily. Increase dose as tolerated to 40 mg daily (2.2).
- Acute Myocardial Infarction (MI): Give 5 mg within 24 hours of MI followed by 5 mg after 24 hours, then 10 mg once daily (2.3).
- Renal Impairment: For patients with creatinine clearance ≥ 10 mL/min and ≤ 30 mL/min, halve usual initial dose. For patients with creatinine clearance < 10 mL/min or on hemodialysis, the recommended initial dose is 2.5 mg (2.4).

3 DOSAGE FORMS AND STRENGTHS

Oral solution: 1 mg/mL (3).

4 CONTRAINDICATIONS

- Angioedema or a history of hereditary or idiopathic angioedema (4).
- Hypersensitivity (4).
- Co-administration of aliskiren with QBRELIS in patients with diabetes (4, 7.4).
- In combination with a neprilysin inhibitor (4).

5 WARNINGS AND PRECAUTIONS

- Angioedema: Discontinue QBRELIS; provide appropriate therapy and monitor until resolved (5.2).
- Renal impairment: Monitor renal function periodically (5.3).
- Hypotension: Patients with other heart or renal diseases have increased risk, monitor blood pressure after initiation (5.4).
- Hyperkalemia: Monitor serum potassium periodically (5.5).
- Cholestatic jaundice and hepatic failure: Monitor for jaundice or signs of liver failure (5.6).

6 ADVERSE REACTIONS

Common adverse reactions (events 2% greater than placebo) by use:

- Hypertension: headache, dizziness and cough (6.1).
- Heart Failure: hypotension and chest pain (6.1).
- Acute Myocardial Infarction: hypotension (6.1).

To report SUSPECTED ADVERSE REACTIONS, contact Azurity Pharmaceuticals, Inc., at 1-800-461-7449 or FDA at 1-800-FDA-1088 or www.fda.gov/medwatch.

7 DRUG INTERACTIONS

- Diuretics: Excessive drop in blood pressure (7.1).
- NSAIDS: Increased risk of renal impairment and loss of antihypertensive efficacy (7.3).
- Dual inhibition of the renin-angiotensin system: Increased risk of renal impairment, hypotension and hyperkalemia (7.4).
- Lithium: Symptoms of lithium toxicity (7.5).
- Gold: Nitritoid reactions have been reported (7.6).

8 USE IN SPECIFIC POPULATIONS

- Lactation: Advise not to breastfeed (8.2).
- Race: Less antihypertensive effect in Blacks than non-Blacks (8.6).

FULL PRESCRIBING INFORMATION

WARNING: FETAL TOXICITY

- When pregnancy is detected, discontinue QBRELIS as soon as possible [see Warnings and Precautions (5.1)] .
- Drugs that act directly on the renin-angiotensin system can cause injury and death to the developing fetus [see Warnings and Precautions (5.1)] .

1 INDICATIONS AND USAGE

1.1 Hypertension

QBRELIS is indicated for the treatment of hypertension in adult patients and pediatric patients 6 years of age and older to lower blood pressure. Lowering blood pressure lowers the risk of fatal and nonfatal cardiovascular events, primarily strokes and myocardial infarctions. These benefits have been seen in controlled trials of antihypertensive drugs from a wide variety of pharmacologic classes.

Control of high blood pressure should be part of comprehensive cardiovascular risk management, including, as appropriate, lipid control, diabetes management, antithrombotic therapy, smoking cessation, exercise, and limited sodium intake. Many patients will require more than 1 drug to achieve blood pressure goals. For specific advice on goals and management, see published guidelines, such as those of the National High Blood Pressure Education Program’s Joint National Committee on Prevention, Detection, Evaluation, and Treatment of High Blood Pressure (JNC).

Numerous antihypertensive drugs from a variety of pharmacologic classes and with different mechanisms of action have been shown in randomized controlled trials to reduce cardiovascular morbidity and mortality, and it can be concluded that it is blood pressure reduction, and not some other pharmacologic property of the drugs, that is largely responsible for those benefits. The largest and most consistent cardiovascular outcome benefit has been a reduction in the risk of stroke, but reductions in myocardial infarction and cardiovascular mortality also have been seen regularly.

Elevated systolic or diastolic pressure causes increased cardiovascular risk, and the absolute risk increase per mmHg is greater at higher blood pressures, so that even modest reductions of severe hypertension can provide substantial benefit. Relative risk reduction from blood pressure reduction is similar across populations with varying absolute risk, so the absolute benefit is greater in patients who are at higher risk independent of their hypertension (for example, patients with diabetes or hyperlipidemia), and such patients would be expected to benefit from more aggressive treatment to a lower blood pressure goal.

Some antihypertensive drugs have smaller blood pressure effects (as monotherapy) in Black patients, and many antihypertensive drugs have additional approved indications and effects (e.g., on angina, heart failure, or diabetic kidney disease). These considerations may guide selection of therapy.

QBRELIS may be administered alone or with other antihypertensive agents [see Clinical Studies (14.1)] .

1.2 Heart Failure

QBRELIS is indicated to reduce signs and symptoms of systolic heart failure [see Clinical Studies (14.2)] .

1.3 Reduction of Mortality in Acute Myocardial Infarction

QBRELIS is indicated for the reduction of mortality in treatment of hemodynamically stable patients within 24 hours of acute myocardial infarction. Patients should receive, as appropriate, the standard recommended treatments such as thrombolytics, aspirin and beta-blockers [see Clinical Studies (14.3)] .

2 DOSAGE AND ADMINISTRATION

2.1 Hypertension

Adults

Initial Therapy in adults: The recommended initial dose is 10 mg taken orally once a day. Adjust dosage as needed according to blood pressure response. The usual dosage range is 20 to 40 mg per day administered in a single daily dose. Doses up to 80 mg per day have been used but do not appear to give greater effect.

Use with diuretics in adults

If blood pressure is not controlled with QBRELIS alone, a low dose of a diuretic may be added (e.g., hydrochlorothiazide, 12.5 mg). After the addition of a diuretic, it may be possible to reduce the dose of QBRELIS.

The recommended starting dose in adult patients with hypertension taking diuretics is 5 mg once per day.

Pediatric Patients 6 years of age and older with hypertension

For pediatric patients with glomerular filtration rate > 30 mL/min/1.73m^2, the recommended starting dose is 0.07 mg per kg (up to 5 mg total) taken orally once daily. Dosage should be adjusted according to blood pressure response up to a maximum of 0.61 mg per kg (up to 40 mg) once daily. Doses above 0.61 mg per kg (or in excess of 40 mg) have not been studied in pediatric patients [see Clinical Pharmacology (12.3)] .

QBRELIS is not recommended in pediatric patients less than 6 years of age or in pediatric patients with glomerular filtration rate < 30 mL/min/1.73m^2 [see Use in Specific Populations (8.4) and Clinical Studies (14.1)].

2.2 Heart Failure

The recommended starting dose for QBRELIS, when used with diuretics and (usually) digitalis as adjunctive therapy for systolic heart failure, is 5 mg taken orally once daily. The recommended starting dose in these patients with hyponatremia (serum sodium < 130 mEq/L) is 2.5 mg once daily. Increase as tolerated to a maximum of 40 mg once daily.

Diuretic dose may need to be adjusted to help minimize hypovolemia, which may contribute to hypotension [see Warnings and Precautions (5.4), and Drug Interactions (7.1)] . The appearance of hypotension after the initial dose of QBRELIS does not preclude subsequent careful dose titration with the drug, following effective management of the hypotension.

2.3 Reduction of Mortality in Acute Myocardial Infarction

Initiation

In hemodynamically stable patients within 24 hours of the onset of symptoms of acute myocardial infarction, give QBRELIS 5 mg orally, followed by 5 mg after 24 hours, and then 10 mg once daily. Dosing should continue for at least six weeks. In patients with a low systolic blood pressure (≤ 120 mmHg and > 100 mmHg) during the first 3 days after the infarct initiate therapy with 2.5 mg once daily [see Warnings and Precautions (5.4)] and titrate up based on tolerability.

Maintenance

The usual maintenance dose is 10 mg once daily. If hypotension (systolic blood pressure ≤ 100 mmHg) occurs during maintenance treatment, give 5 mg once daily with temporary reductions to 2.5 mg if needed. If prolonged hypotension occurs (systolic blood pressure < 90 mmHg for more than 1 hour) QBRELIS should be withdrawn.

2.4 Dose in Patients with Renal Impairment

No dose adjustment of QBRELIS is required in patients with creatinine clearance > 30 mL/min. In patients with creatinine clearance ≥ 10 mL/min and ≤ 30 mL/min, reduce the initial dose of QBRELIS to half of the usual recommended dose, i.e., hypertension, 5 mg once daily; systolic heart failure, 2.5 mg once daily and acute myocardial infarction, 2.5 mg once daily. Up titrate as tolerated to a maximum of 40 mg daily. For patients on hemodialysis or creatinine clearance < 10 mL/min, the recommended initial dose is 2.5 mg once daily [see Use in Specific Populations (8.7) and Clinical Pharmacology (12.3)] .

3 DOSAGE FORMS AND STRENGTHS

QBRELIS oral solution is available in a 150 mL bottle containing 1 mg/mL of lisinopril solution. QBRELIS oral solution is a clear to slightly opalescent liquid.

4 CONTRAINDICATIONS

QBRELIS is contraindicated in patients with:

- a history of angioedema or hypersensitivity related to previous treatment with an angiotensin converting enzyme inhibitor
- hereditary or idiopathic angioedema

Do not co-administer aliskiren with QBRELIS in patients with diabetes [see Drug Interactions (7.4)] .

QBRELIS is contraindicated in combination with a neprilysin inhibitor (e.g., sacubitril). Do not administer QBRELIS within 36 hours of switching to or from sacubitril/valsartan, a neprilysin inhibitor [see Warnings and Precautions (5.2)] .

5 WARNINGS AND PRECAUTIONS

5.1 Fetal Toxicity

Use of drugs that act on the renin-angiotensin system during the second and third trimesters of pregnancy reduces fetal renal function and increases fetal and neonatal morbidity and death. Resulting oligohydramnios can be associated with fetal lung hypoplasia and skeletal deformations. Potential neonatal adverse effects include skull hypoplasia, anuria, hypotension, renal failure, and death. When pregnancy is detected, discontinue QBRELIS as soon as possible [see Use in Specific Populations (8.1)].

5.2 Angioedema and Anaphylactoid Reactions

Angioedema

Head and Neck Angioedema

Angioedema of the face, extremities, lips, tongue, glottis and/or larynx, including some fatal reactions, have occurred in patients treated with angiotensin converting enzyme inhibitors, including lisinopril, at any time during treatment. Patients with involvement of the tongue, glottis or larynx are likely to experience airway obstruction, especially those with a history of airway surgery. QBRELIS should be promptly discontinued and appropriate therapy and monitoring should be provided until complete and sustained resolution of signs and symptoms of angioedema has occurred.

Patients with a history of angioedema unrelated to ACE inhibitor therapy may be at increased risk of angioedema while receiving an ACE inhibitor [see Contraindications (4)] . ACE inhibitors have been associated with a higher rate of angioedema in Black than in non-Black patients.

Patients receiving coadministration of an ACE inhibitor and mTOR (mammalian target of rapamycin) inhibitor (e.g., temsirolimus, sirolimus, everolimus) therapy or a neprilysin inhibitor may be at increased risk for angioedema [see Drug Interactions (7.7, 7.8)] .

Intestinal Angioedema

Intestinal angioedema has occurred in patients treated with ACE inhibitors. These patients presented with abdominal pain (with or without nausea or vomiting); in some cases there was no prior history of facial angioedema and C-1 esterase levels were normal. In some cases, the angioedema was diagnosed by procedures including abdominal CT scan or ultrasound, or at surgery, and symptoms resolved after stopping the ACE inhibitor.

Anaphylactoid Reactions

Anaphylactoid Reactions During Desensitization

Two patients undergoing desensitizing treatment with hymenoptera venom while receiving ACE inhibitors sustained life-threatening anaphylactoid reactions.

Anaphylactoid Reactions During Dialysis

Sudden and potentially life threatening anaphylactoid reactions have occurred in some patients dialyzed with high-flux membranes and treated concomitantly with an ACE inhibitor. In such patients, dialysis must be stopped immediately, and aggressive therapy for anaphylactoid reactions must be initiated. Symptoms have not been relieved by antihistamines in these situations. In these patients, consideration should be given to using a different type of dialysis membrane or a different class of antihypertensive agent. Anaphylactoid reactions have also been reported in patients undergoing low-density lipoprotein apheresis with dextran sulfate absorption.

5.3 Impaired Renal Function

Monitor renal function periodically in patients treated with QBRELIS. Changes in renal function including acute renal failure can be caused by drugs that inhibit the renin-angiotensin system. Patients whose renal function may depend in part on the activity of the renin-angiotensin system (e.g., patients with renal artery stenosis, chronic kidney disease, severe congestive heart failure, post-myocardial infarction or volume depletion) may be at particular risk of developing acute renal failure on QBRELIS. Consider withholding or discontinuing therapy in patients who develop a clinically significant decrease in renal function on QBRELIS [see Adverse Reactions (6.1) and Drug Interactions (7.4)] .

5.4 Hypotension

QBRELIS can cause symptomatic hypotension, sometimes complicated by oliguria, progressive azotemia, acute renal failure or death. Patients at risk of excessive hypotension include those with the following conditions or characteristics: heart failure with systolic blood pressure below 100 mmHg, ischemic heart disease, cerebrovascular disease, hyponatremia, high dose diuretic therapy, renal dialysis, or severe volume and/or salt depletion of any etiology.

In these patients, QBRELIS should be started under very close medical supervision and such patients should be followed closely for the first two weeks of treatment and whenever the dose of QBRELIS and/or diuretic is increased. Avoid use of QBRELIS in patients who are hemodynamically unstable after acute MI.

Symptomatic hypotension is also possible in patients with severe aortic stenosis or hypertrophic cardiomyopathy.

Surgery/Anesthesia

In patients undergoing major surgery or during anesthesia with agents that produce hypotension, QBRELIS may block angiotensin II formation secondary to compensatory renin release. If hypotension occurs and is considered to be due to this mechanism, it can be corrected by volume expansion.

5.5 Hyperkalemia

Serum potassium should be monitored periodically in patients receiving QBRELIS. Drugs that inhibit the renin-angiotensin system can cause hyperkalemia. Risk factors for the development of hyperkalemia include renal insufficiency, diabetes mellitus, and the concomitant use of potassium-sparing diuretics, potassium supplements and/or potassium-containing salt substitutes [see Drug Interactions (7.1)] .

5.6 Hepatic Failure

ACE inhibitors have been associated with a syndrome that starts with cholestatic jaundice or hepatitis and progresses to fulminant hepatic necrosis and sometimes death. The mechanism of this syndrome is not understood. Patients receiving ACE inhibitors who develop jaundice or marked elevations of hepatic enzymes should discontinue the ACE inhibitor and receive appropriate medical treatment.

6 ADVERSE REACTIONS

6.1 Clinical Trials Experience

Because clinical trials are conducted under widely varying conditions, adverse reaction rates observed in the clinical studies of a drug cannot be directly compared to rates in the clinical studies of another drug and may not reflect the rates observed in practice.

Hypertension

In clinical trials in patients with hypertension treated with lisinopril, 5.7% of patients on lisinopril discontinued with adverse reactions.

The following adverse reactions (events 2% greater on lisinopril than on placebo) were observed with lisinopril alone: headache (by 3.8%), dizziness (by 3.5%), and cough (by 2.5%).

Heart Failure

In patients with systolic heart failure treated with lisinopril for up to four years, 11% discontinued therapy with adverse reactions. In controlled studies in patients with heart failure, therapy was discontinued in 8.1% of patients treated with lisinopril for 12 weeks, compared to 7.7% of patients treated with placebo for 12 weeks.

The following adverse reactions (events 2% greater on lisinopril than on placebo) were observed with lisinopril: hypotension (by 3.8%), and chest pain (by 2.1%).

In the two-dose ATLAS trial [see Clinical Studies (14.2)] in heart failure patients, withdrawals due to adverse reactions were not different between the low and high dose groups, either in total number of discontinuation (17-18%) or in rare specific reactions (< 1%). The following adverse reactions, mostly related to ACE inhibition, were reported more commonly in the high dose group:

Table 1. Dose-related Adverse Drug Reactions: ATLAS trial
 | High Dose (n=1568) | Low Dose (n=1596)
Dizziness | 19% | 12%
Hypotension | 11% | 7%
Creatinine increased | 10% | 7%
Hyperkalemia | 6% | 4%
Syncope | 7% | 5%

Acute Myocardial Infarction

Patients treated with lisinopril had a higher incidence of hypotension (by 5.3%) and renal dysfunction (by 1.3%) compared with patients not taking lisinopril.

Other clinical adverse reactions occurring in 1% or higher of patients with hypertension or heart failure treated with lisinopril in controlled clinical trials and do not appear in other sections of labeling are listed below:

Body as a whole:Fatigue, asthenia, orthostatic effects.

Digestive:Pancreatitis, constipation, flatulence, dry mouth, diarrhea.

Hematologic:Rare cases of bone marrow depression, hemolytic anemia, leukopenia/neutropenia and thrombocytopenia.

Endocrine:Diabetes mellitus, inappropriate antidiuretic hormone secretion.

Metabolic:Gout.

Skin:Urticaria, alopecia, photosensitivity, erythema, flushing, diaphoresis, cutaneous pseudolymphoma, toxic epidermal necrolysis, Stevens - Johnson syndrome, and pruritus.

Special Senses:Visual loss, diplopia, blurred vision, tinnitus, photophobia, taste disturbances, olfactory disturbance.

Urogenital:Impotence.

Miscellaneous:A symptom complex has been reported which may include a positive ANA, an elevated erythrocyte sedimentation rate, arthralgia/arthritis, myalgia, fever, vasculitis, eosinophilia, leukocytosis, paresthesia and vertigo. Rash, photosensitivity or other dermatological manifestations may occur alone or in combination with these symptoms.

Clinical Laboratory Test Findings

Serum Potassium:In clinical trials hyperkalemia (serum potassium greater than 5.7 mEq/L) occurred in 2.2% and 4.8% of lisinopril-treated patients with hypertension and heart failure, respectively [see Warnings and Precautions (5.5)] .

Creatinine, Blood Urea Nitrogen:Minor increases in blood urea nitrogen and serum creatinine, reversible upon discontinuation of therapy, were observed in about 2% of patients with hypertension treated with lisinopril alone. Increases were more common in patients receiving concomitant diuretics and in patients with renal artery stenosis [see Warnings and Precautions (5.4)] . Reversible minor increases in blood urea nitrogen and serum creatinine were observed in 11.6% of patients with heart failure on concomitant diuretic therapy. Frequently, these abnormalities resolved when the dosage of the diuretic was decreased.

Patients with acute myocardial infarction in the GISSI-3 trial treated with lisinopril had a higher (2.4% versus 1.1% in placebo) incidence of renal dysfunction in-hospital and at six weeks (increasing creatinine concentration to over 3 mg/dL or a doubling or more of the baseline serum creatinine concentration).

Hemoglobin and Hematocrit:Small decreases in hemoglobin and hematocrit (mean decreases of approximately 0.4 g% and 1.3 vol%, respectively) occurred frequently in patients treated with lisinopril but were rarely of clinical importance in patients without some other cause of anemia. In clinical trials, less than 0.1% of patients discontinued therapy due to anemia.

6.2 Post-marketing Experience

The following adverse reactions have been identified during post-approval use of lisinopril that are not included in other sections of labeling. Because these reactions are reported voluntarily from a population of uncertain size, it is not always possible to reliably estimate their frequency or establish a causal relationship to drug exposure.

Other reactions include:

Metabolism and nutrition disorders

Hyponatremia [see Warnings and Precautions (5.4)] , cases of hypoglycemia in diabetic patients on oral antidiabetic agents or insulin [see Drug Interactions (7.2)] .

Nervous system and psychiatric disorders

Mood alterations (including depressive symptoms), mental confusion, hallucinations

Skin and subcutaneous tissue disorders

Psoriasis

7 DRUG INTERACTIONS

7.1 Diuretics

Initiation of QBRELIS in patients on diuretics may result in excessive reduction of blood pressure. The possibility of hypotensive effects with QBRELIS can be minimized by either decreasing or discontinuing the diuretic or increasing the salt intake prior to initiation of treatment with QBRELIS. If this is not possible, reduce the starting dose of QBRELIS [see Dosage and Administration (2.2) and Warnings and Precautions (5.4)] .

QBRELIS attenuates potassium loss caused by thiazide-type diuretics. Potassium-sparing diuretics (spironolactone, amiloride, triamterene, and others) can increase the risk of hyperkalemia. Therefore, if concomitant use of such agents is indicated, monitor the patient’s serum potassium frequently.

7.2 Antidiabetics

Concomitant administration of QBRELIS and antidiabetic medicines (insulins, oral hypoglycemic agents) may cause an increased blood-glucose-lowering effect with risk of hypoglycemia.

7.3 Non-Steroidal Anti-Inflammatory Agents Including Selective Cyclooxygenase-2 Inhibitors (COX-2 Inhibitors)

In patients who are elderly, volume-depleted (including those on diuretic therapy), or with compromised renal function, co-administration of NSAIDs, including selective COX-2 inhibitors, with ACE inhibitors, including lisinopril, may result in deterioration of renal function, including possible acute renal failure. These effects are usually reversible. Monitor renal function periodically in patients receiving lisinopril and NSAID therapy.

The antihypertensive effect of ACE inhibitors, including lisinopril, may be attenuated by NSAIDs.

7.4 Dual Blockade of the Renin-Angiotensin System (RAS)

Dual blockade of the RAS with angiotensin receptor blockers, ACE inhibitors, or aliskiren is associated with increased risks of hypotension, hyperkalemia, and changes in renal function (including acute renal failure) compared to monotherapy.

The VA NEPHRON trial enrolled 1448 patients with type 2 diabetes, elevated urinary-albumin-to-creatinine ratio, and decreased estimated glomerular filtration rate (GFR 30 to 89.9 mL/min), randomized them to lisinopril or placebo on a background of losartan therapy and followed them for a median of 2.2 years. Patients receiving the combination of losartan and lisinopril did not obtain any additional benefit compared to monotherapy for the combined endpoint of decline in GFR, end stage renal disease, or death, but experienced an increased incidence of hyperkalemia and acute kidney injury compared with the monotherapy group.

In general, avoid combined use of RAS inhibitors. Closely monitor blood pressure, renal function and electrolytes in patients on QBRELIS and other agents that affect the RAS.

Do not co-administer aliskiren with QBRELIS in patients with diabetes. Avoid use of aliskiren with QBRELIS in patients with renal impairment (GFR < 60 mL/min).

7.5 Lithium

Lithium toxicity has been reported in patients receiving lithium concomitantly with drugs, which cause elimination of sodium, including ACE inhibitors. Lithium toxicity was usually reversible upon discontinuation of lithium and the ACE inhibitor. Monitor serum lithium levels during concurrent use.

7.6 Gold

Nitritoid reactions (symptoms include facial flushing, nausea, vomiting and hypotension) have been reported rarely in patients on therapy with injectable gold (sodium aurothiomalate) and concomitant ACE inhibitor therapy including lisinopril.

7.7 mTOR Inhibitors

Patients taking concomitant mTOR inhibitor (e.g., temsirolimus, sirolimus, everolimus) therapy may be at increased risk for angioedema [see Warnings and Precautions (5.2)] .

7.8 Neprilysin Inhibitor

Patients taking concomitant neprilysin inhibitors may be at increased risk for angioedema [see Warnings and Precautions (5.2)].

8 USE IN SPECIFIC POPULATIONS

8.1 Pregnancy

Risk Summary

QBRELIS can cause fetal harm when administered to a pregnant woman. Use of drugs that act on the renin-angiotensin system during the second and third trimesters of pregnancy reduces fetal renal function and increases fetal and neonatal morbidity and death. Most epidemiologic studies examining fetal abnormalities after exposure to antihypertensive use in the first trimester have not distinguished drugs affecting the renin-angiotensin system from other antihypertensive agents. When pregnancy is detected, discontinue QBRELIS as soon as possible.

The estimated background risk of major birth defects and miscarriage for the indicated population(s) are unknown. In the general U.S. population, the estimated background risk of major birth defects and miscarriage in clinically recognized pregnancies is 2-4% and 15-20%, respectively.

Clinical Considerations

Disease-associated maternal and/or embryo/fetal risk

Hypertension in pregnancy increases the maternal risk for pre-eclampsia, gestational diabetes, premature delivery, and delivery complications (e.g., need for cesarean section, and post-partum hemorrhage). Hypertension increases the fetal risk for intrauterine growth restriction and intrauterine death. Pregnant women with hypertension should be carefully monitored and managed accordingly.

Fetal/Neonatal Adverse Reactions

Oligohydramnios in pregnant women who use drugs affecting the renin-angiotensin system in the second and third trimesters of pregnancy can result in the following: reduced fetal renal function leading to anuria and renal failure, fetal lung hypoplasia and skeletal deformations, including skull hypoplasia, hypotension, and death. In the unusual case that there is no appropriate alternative to therapy with drugs affecting the renin-angiotensin system for a particular patient, apprise the mother of the potential risk to the fetus.

Perform serial ultrasound examinations to assess the intra-amniotic environment. Fetal testing may be appropriate, based on the week of pregnancy. Patients and physicians should be aware, however, that oligohydramnios may not appear until after the fetus has sustained irreversible injury. Closely observe infants with histories of in uteroexposure to QBRELIS for hypotension, oliguria, and hyperkalemia. If oliguria or hypotension occur in neonates with a history of in uteroexposure to QBRELIS, support blood pressure and renal perfusion. Exchange transfusions or dialysis may be required as a means of reversing hypotension and substituting for disordered renal function.

8.2 Lactation

Risk Summary

No data are available regarding the presence of lisinopril in human milk or the effects of lisinopril on the breastfed infant or on milk production. Lisinopril is present in rat milk. Because of the potential for severe adverse reactions in the breastfed infant, advise women not to breastfeed during treatment with QBRELIS.

8.4 Pediatric Use

Antihypertensive effects and safety of lisinopril have been established in pediatric patients aged 6 to 16 years [see Dosage and Administration (2.1) and Clinical Studies (14.1)] . No relevant differences between the adverse reaction profile for pediatric patients and adult patients were identified.

Safety and effectiveness of lisinopril have not been established in pediatric patients under the age 6 or in pediatric patients with glomerular filtration rate < 30 mL/min/1.73 m^2 [see Dosage and Administration (2.1), Clinical Pharmacology (12.3), and Clinical Studies (14.1)] .

Neonates with a history of in utero exposure to QBRELIS

If oliguria or hypotension occurs, direct attention toward support of blood pressure and renal perfusion. Exchange transfusions or dialysis may be required as a means of reversing hypotension and/or substituting for disordered renal function.

8.5 Geriatric Use

No dosage adjustment with QBRELIS is necessary in elderly patients. In a clinical study of lisinopril in patients with myocardial infarctions (GISSI-3 Trial), 4,413 (47%) were 65 and over, while 1,656 (18%) were 75 and over. In this study, 4.8 % of patients aged 75 years and older discontinued lisinopril treatment because of renal dysfunction vs. 1.3% of patients younger than 75 years. No other differences in safety or effectiveness were observed between elderly and younger patients, but greater sensitivity of some older individuals cannot be ruled out.

8.6 Race

ACE inhibitors, including QBRELIS, have an effect on blood pressure that is less in Black patients than in non-Blacks.

8.7 Renal Impairment

Dose adjustment of QBRELIS is required in patients undergoing hemodialysis or whose creatinine clearance is ≤ 30 mL/min. No dose adjustment of QBRELIS is required in patients with creatinine clearance > 30 mL/min [see Dosage and Administration (2.4) and Clinical Pharmacology (12.3)] .

10 OVERDOSAGE

Following a single oral dose of 20 g/kg no lethality occurred in rats, and death occurred in one of 20 mice receiving the same dose. The most likely manifestation of overdosage would be hypotension, for which the usual treatment would be intravenous infusion of normal saline solution.

Lisinopril can be removed by hemodialysis [see Clinical Pharmacology (12.3)] .

11 DESCRIPTION

Lisinopril is an oral long-acting angiotensin converting enzyme (ACE) inhibitor. Lisinopril is a synthetic peptide derivative that is manufactured as a dihydrate and is chemically described as 1-[ N^2-[(S)-1-Carboxy-3-phenylpropyl]-L-lysyl]-L-proline dihydrate. Its molecular formula is C21H31N3O5·2H2O and its structural formula is:

Lisinopril is a white to off-white, crystalline powder, with a molecular weight of 441.52 (for dihydrate). It is soluble in water, sparingly soluble in methanol, and practically insoluble in ethanol.

QBRELIS (lisinopril), 1 mg/mL, is a ready-to-use aqueous formulation. Each 1 mL of the oral solution contains 1.09 mg of lisinopril dihydrate, which is equivalent to 1 mg of lisinopril as the active ingredient and the following inactive ingredients: purified water, xylitol, sodium citrate, citric acid, sodium benzoate, and either hydrochloric acid or sodium hydroxide which may be added for pH adjustment. The solution is clear to slightly opalescent. The pH of the solution ranges from 4.3 to 5.1. QBRELIS is supplied as 150 mL of the solution packaged in a 150-mL round, white, opaque, high-density polyethylene (HDPE) bottle with a white, polypropylene, child-resistant closure with a heat induction layered inner seal.

12 CLINICAL PHARMACOLOGY

12.1 Mechanism of Action

Lisinopril inhibits angiotensin-converting enzyme (ACE) in human subjects and animals. ACE is a peptidyl dipeptidase that catalyzes the conversion of angiotensin I to the vasoconstrictor substance, angiotensin II. Angiotensin II also stimulates aldosterone secretion by the adrenal cortex. The beneficial effects of lisinopril in hypertension and heart failure appear to result primarily from suppression of the renin-angiotensin-aldosterone system. Inhibition of ACE results in decreased plasma angiotensin II which leads to decreased vasopressor activity and to decreased aldosterone secretion. The latter decrease may result in a small increase of serum potassium. In hypertensive patients with normal renal function treated with lisinopril alone for up to 24 weeks, the mean increase in serum potassium was approximately 0.1 mEq/L; however, approximately 15% of patients had increases greater than 0.5 mEq/L and approximately 6% had a decrease greater than 0.5 mEq/L. In the same study, patients treated with lisinopril and hydrochlorothiazide for up to 24 weeks had a mean decrease in serum potassium of 0.1 mEq/L; approximately 4% of patients had increases greater than 0.5 mEq/L and approximately 12% had a decrease greater than 0.5 mEq/L [see Clinical Studies (14.1)] . Removal of angiotensin II negative feedback on renin secretion leads to increased plasma renin activity.

ACE is identical to kininase, an enzyme that degrades bradykinin. Whether increased levels of bradykinin, a potent vasodepressor peptide, play a role in the therapeutic effects of QBRELIS remains to be elucidated.

While the mechanism through which QBRELIS lowers blood pressure is believed to be primarily suppression of the renin-angiotensin-aldosterone system, QBRELIS is antihypertensive even in patients with low-renin hypertension. Although lisinopril was antihypertensive in all races studied, Black hypertensive patients (usually a low‑renin hypertensive population) had a smaller average response to monotherapy than non-Black patients.

Concomitant administration of lisinopril and hydrochlorothiazide further reduced blood pressure in Black and non-Black patients and any racial differences in blood pressure response were no longer evident.

12.2 Pharmacodynamics

Hypertension

Adult Patients: Administration of lisinopril to patients with hypertension results in a reduction of both supine and standing blood pressure to about the same extent with no compensatory tachycardia. Symptomatic postural hypotension is usually not observed although it can occur and should be anticipated in volume and/or salt-depleted patients [see Warnings and Precautions (5.4)] . When given together with thiazide-type diuretics, the blood pressure lowering effects of the two drugs are approximately additive.

In most patients studied, onset of antihypertensive activity was seen at one hour after oral administration of an individual dose of lisinopril, with peak reduction of blood pressure achieved by 6 hours. Although an antihypertensive effect was observed 24 hours after dosing with recommended single daily doses, the effect was more consistent and the mean effect was considerably larger in some studies with doses of 20 mg or more than with lower doses; however, at all doses studied, the mean antihypertensive effect was substantially smaller 24 hours after dosing than it was 6 hours after dosing.

The antihypertensive effects of lisinopril are maintained during long-term therapy. Abrupt withdrawal of lisinopril has not been associated with a rapid increase in blood pressure, or a significant increase in blood pressure compared to pretreatment levels.

Non-Steroidal Anti-Inflammatory Agents

In a study in 36 patients with mild to moderate hypertension where the antihypertensive effects of lisinopril alone were compared lisinopril given concomitantly with indomethacin, the use of indomethacin was associated with a reduced effect, although the difference between the two regimens was not significant.

12.3 Pharmacokinetics

Adult Patients: QBRELIS is bioequivalent to lisinopril tablets under fasted and fed conditions.

Following oral administration of lisinopril tablets, peak serum concentrations of lisinopril occur within about 7 hours, although there was a trend to a small delay in time taken to reach peak serum concentrations in acute myocardial infarction patients. Food does not alter the bioavailability of lisinopril tablets. Declining serum concentrations exhibit a prolonged terminal phase, which does not contribute to drug accumulation. This terminal phase probably represents saturable binding to ACE and is not proportional to dose. Upon multiple dosing, lisinopril exhibits an effective half-life of 12 hours.

Lisinopril does not appear to be bound to other serum proteins. Lisinopril does not undergo metabolism and is excreted unchanged entirely in the urine. Based on urinary recovery, the mean extent of absorption of lisinopril is approximately 25%, with large intersubject variability (6‑60%) at all doses tested (5‑80 mg). The absolute bioavailability of lisinopril is reduced to 16% in patients with stable NYHA Class II-IV congestive heart failure, and the volume of distribution appears to be slightly smaller than that in normal subjects. The oral bioavailability of lisinopril in patients with acute myocardial infarction is similar to that in healthy volunteers.

Impaired renal function decreases elimination of lisinopril, which is excreted principally through the kidneys, but this decrease becomes clinically important only when the glomerular filtration rate is below 30 mL/min. Above this glomerular filtration rate, the elimination half-life is little changed. With greater impairment, however, peak and trough lisinopril levels increase, time to peak concentration increases and time to attain steady state is prolonged [see Dosage and Administration (2.4)] . Lisinopril can be removed by hemodialysis.

Pediatric Patients:The pharmacokinetics of lisinopril were studied in 29 pediatric hypertensive patients between 6 years and 16 years with glomerular filtration rate > 30 mL/min/1.73 m^2. After doses of 0.1 to 0.2 mg per kg, steady state peak plasma concentrations of lisinopril occurred within 6 hours and the extent of absorption based on urinary recovery was about 28%. These values are similar to those obtained previously in adults. The typical value of lisinopril oral clearance (systemic clearance/absolute bioavailability) in a child weighing 30 kg is 10 L/h, which increases in proportion to renal function.

13 NONCLINICAL TOXICOLOGY

13.1 Carcinogenesis, Mutagenesis, Impairment of Fertility

There was no evidence of a tumorigenic effect when lisinopril was administered for 105 weeks to male and female rats at doses up to 90 mg per kg per day (about 56 or 9 times* the maximum recommended daily human dose, based on body weight and body surface area, respectively). There was no evidence of carcinogenicity when lisinopril was administered for 92 weeks to (male and female) mice at doses up to 135 mg per kg per day (about 84 times* the maximum recommended daily human dose). This dose was 6.8 times the maximum human dose based on body surface area in mice.

Lisinopril was not mutagenic in the Ames microbial mutagen test with or without metabolic activation. It was also negative in a forward mutation assay using Chinese hamster lung cells. Lisinopril did not produce single strand DNA breaks in an in vitroalkaline elution rat hepatocyte assay. In addition, lisinopril did not produce increases in chromosomal aberrations in an in vitrotest in Chinese hamster ovary cells or in an in vivostudy in mouse bone marrow.

There were no adverse effects on reproductive performance in male and female rats treated with up to 300 mg per kg per day of lisinopril. This dose is 188 times and 30 times the maximum human dose when based on mg/kg and mg/m^2, respectively.

Studies in rats indicate that lisinopril crosses the blood brain barrier poorly. Multiple doses of lisinopril in rats do not result in accumulation in any tissues. Milk of lactating rats contains radioactivity following administration of^14C lisinopril. By whole body autoradiography, radioactivity was found in the placenta following administration of labeled drug to pregnant rats, but none was found in the fetuses.

*Calculations assume a human weight of 50 kg and human body surface area of 1.62 m^2.

14 CLINICAL STUDIES

14.1 Hypertension

Two dose-response studies utilizing a once-daily regimen were conducted in 438 mild to moderate hypertensive patients not on a diuretic. Blood pressure was measured 24 hours after dosing. An antihypertensive effect of lisinopril was seen with 5 mg of lisinopril in some patients. However, in both studies blood pressure reduction occurred sooner and was greater in patients treated with 10, 20 or 80 mg of lisinopril than patients treated with 5 mg of lisinopril.

In controlled clinical studies of patients with mild to moderate hypertension, patients were treated with lisinopril 20-80 mg daily, hydrochlorothiazide 12.5-50 mg daily or atenolol 50‑200 mg daily; and in other studies of patients with moderate to severe hypertension, patients were treated with lisinopril 20-80 mg daily or metoprolol 100-200 mg daily. Lisinopril demonstrated superior reductions of systolic and diastolic compared to hydrochlorothiazide in a population that was 75% Caucasian. Lisinopril was approximately equivalent to atenolol and metoprolol in reducing diastolic blood pressure, and had somewhat greater effects on systolic blood pressure.

Lisinopril had similar blood pressure reductions and adverse effects in younger and older (> 65 years) patients. It was less effective in reducing blood pressure in Blacks than in Caucasians.

In hemodynamic studies of lisinopril in patients with essential hypertension, blood pressure reduction was accompanied by a reduction in peripheral arterial resistance with little or no change in cardiac output and in heart rate. In a study in nine hypertensive patients, following administration of lisinopril, there was an increase in mean renal blood flow that was not significant. Data from several small studies are inconsistent with respect to the effect of lisinopril on glomerular filtration rate in hypertensive patients with normal renal function, but suggest that changes, if any, are not large.

In patients with renovascular hypertension lisinopril has been shown to be well-tolerated and effective in reducing blood pressure [see Warnings and Precautions (5.3)] .

Pediatric Patients:In a clinical study involving 115 hypertensive pediatric patients 6 to 16 years of age, patients who weighed < 50 kg received either 0.625, 2.5 or 20 mg of lisinopril once daily and patients who weighed ≥ 50 kg received either 1.25, 5, or 40 mg of lisinopril once daily. At the end of 2 weeks, lisinopril lowered trough blood pressure in a dose-dependent manner with antihypertensive efficacy demonstrated at doses > 1.25 mg (0.02 mg per kg). This effect was confirmed in a randomized withdrawal phase, where the diastolic pressure rose by about 9 mmHg more in patients randomized to placebo than compared to patients who remained on the middle and high doses of lisinopril. The dose-dependent antihypertensive effect of lisinopril was consistent across several demographic subgroups: age, Tanner stage, gender, and race. In this study, lisinopril was generally well-tolerated.

In the above pediatric study, lisinopril was given either as tablets or in a suspension for those children who were unable to swallow tablets or who required a lower dose than is available in tablet form.

14.2 Heart Failure

Two placebo controlled, 12-week clinical studies compared the addition of lisinopril up to 20 mg daily to digitalis and diuretics alone. The combination of lisinopril, digitalis and diuretics reduced the following signs and symptoms of heart failure: edema, rales, paroxysmal nocturnal dyspnea and jugular venous distention. In one of the studies, the combination of lisinopril, digitalis and diuretics reduced orthopnea, presence of third heart sound and the number of patients classified as NYHA Class III and IV; and improved exercise tolerance. A large (over 3000 patients) survival study, the ATLAS Trial, comparing 2.5 and 35 mg of lisinopril in patients with systolic heart failure, showed that the higher dose of lisinopril had outcomes at least as favorable as the lower dose.

During baseline-controlled clinical trials, in patients with systolic heart failure receiving digitalis and diuretics, single doses of lisinopril resulted in decreases in pulmonary capillary wedge pressure, systemic vascular resistance and blood pressure accompanied by an increase in cardiac output and no change in heart rate.

14.3 Acute Myocardial Infarction

The Gruppo Italiano per lo Studio della Sopravvienza nell’Infarto Miocardico (GISSI-3) study was a multicenter, controlled, randomized, unblinded clinical trial conducted in 19,394 patients with acute myocardial infarction (MI) admitted to a coronary care unit. It was designed to examine the effects of short-term (6 week) treatment with lisinopril, nitrates, their combination, or no therapy on short-term (6 week) mortality and on long-term death and markedly impaired cardiac function. Hemodynamically-stable patients presenting within 24 hours of the onset of symptoms were randomized, in a 2 x 2 factorial design, to six weeks of either 1) lisinopril alone (n=4841), 2) nitrates alone (n=4869), 3) lisinopril plus nitrates (n=4841), or 4) open control (n=4843). All patients received routine therapies, including thrombolytics (72%), aspirin (84%), and a beta blocker (31%), as appropriate, normally utilized in acute myocardial infarction (MI) patients.

The protocol excluded patients with hypotension (systolic blood pressure ≤ 100 mmHg), severe heart failure, cardiogenic shock, and renal dysfunction (serum creatinine > 2 mg per dL and/or proteinuria > 500 mg per 24 h). Patients randomized to lisinopril received 5 mg within 24 hours of the onset of symptoms, 5 mg after 24 hours, and then 10 mg daily thereafter. Patients with systolic blood pressure less than 120 mmHg at baseline received 2.5 mg of lisinopril. If hypotension occurred, the lisinopril dose was reduced or if severe hypotension occurred lisinopril was stopped [see Dosage and Administration (2.3)] .

The primary outcomes of the trial were the overall mortality at 6 weeks and a combined end point at 6 months after the myocardial infarction, consisting of the number of patients who died, had late (day 4) clinical congestive heart failure, or had extensive left ventricular damage defined as ejection fraction ≤ 35% or an akinetic-dyskinetic [A-D] score ≥ 45%. Patients receiving lisinopril (n=9646), alone or with nitrates, had an 11% lower risk of death (p=0.04) compared to patients who did not receive lisinopril (n=9672) (6.4% vs. 7.2%, respectively) at six weeks. Although patients randomized to receive lisinopril for up to six weeks also fared numerically better on the combined end point at 6 months, the open nature of the assessment of heart failure, substantial loss to follow-up echocardiography, and substantial excess use of lisinopril between 6 weeks and 6 months in the group randomized to 6 weeks of lisinopril, preclude any conclusion about this end point.

Patients with acute myocardial infarction, treated with lisinopril, had a higher (9.0% versus 3.7%) incidence of persistent hypotension (systolic blood pressure < 90 mmHg for more than 1 hour) and renal dysfunction (2.4% versus 1.1%) in-hospital and at six weeks (increasing creatinine concentration to over 3 mg per dL or a doubling or more of the baseline serum creatinine concentration) [see Adverse Reactions (6.1)] .

16 HOW SUPPLIED/STORAGE AND HANDLING

QBRELIS (lisinopril), 1 mg/mL, is supplied as 150 mL of a clear to slightly opalescent, colorless aqueous oral solution with a sweet taste in a 150-mL high-density polyethylene (HDPE) bottle with a child-resistant cap (NDC 52652-3001-1).

Store at controlled room temperature 20°C-25°C (68°F-77°F) [see USP] in a tightly closed container. Protect from freezing and excessive heat.

17 PATIENT COUNSELING INFORMATION

Pregnancy: Tell female patients of childbearing age about the consequences of exposure to QBRELIS during pregnancy. Discuss treatment options with women planning to become pregnant. Tell patients to report pregnancies to their physicians as soon as possible.

Angioedema: Angioedema, including laryngeal edema may occur at any time during treatment with angiotensin converting enzyme inhibitors, including QBRELIS. Tell patients to report immediately any signs or symptoms suggesting angioedema (swelling of face, extremities, eyes, lips, tongue, difficulty swallowing or breathing) and to take no more drug until they have consulted with the prescribing physician.

Symptomatic Hypotension: Tell patients to report light-headedness especially during the first few days of therapy. If actual syncope occurs, tell the patient to discontinue the drug until they have consulted with the prescribing physician.

Tell patients that excessive perspiration and dehydration may lead to an excessive fall in blood pressure because of reduction in fluid volume. Other causes of volume depletion such as vomiting or diarrhea may also lead to a fall in blood pressure; advise patients accordingly.

Hyperkalemia: Tell patients to consult their physician prior to using salt substitutes containing potassium.

Hypoglycemia: Tell diabetic patients treated with oral antidiabetic agents or insulin starting an ACE inhibitor to monitor for hypoglycemia closely, especially during the first month of combined use [see Drug Interactions (7.2)] .

Leukopenia/Neutropenia: Tell patients to report promptly any indication of infection (e.g., sore throat, fever), which may be a sign of leukopenia/neutropenia.

Manufactured for:
Azurity Pharmaceuticals, Inc.
Woburn, MA 01801 USA

Patent: https://azurity.com/patents

This product’s label may have been updated. For current Full Prescribing Information, please visit Qbrelis.com

PI100073.05 Rev. 4/2023

PRINCIPAL DISPLAY PANEL - Bottle Label

NDC 52652-3001-1

Qbrelis®
(lisinopril)

Oral Solution
1 mg/mL

READY TO USE

150 mL
azurity™
pharmaceuticals
Rx Only

Each 1 mL contains
1 mg of lisinopril.

Usual Dose:
See prescribing information.

Store at room temperature
20° - 25°C (68° - 77°F)
Avoid freezing and excessive heat.
Keep container tightly closed.

KEEP THIS AND ALL
MEDICATIONS OUT OF THE
REACH OF CHILDREN

P/N 141146

Manufactured for:
Azurity Pharmaceuticals, Inc.
Wilmington, MA 01887 USA

Lot:
Exp: